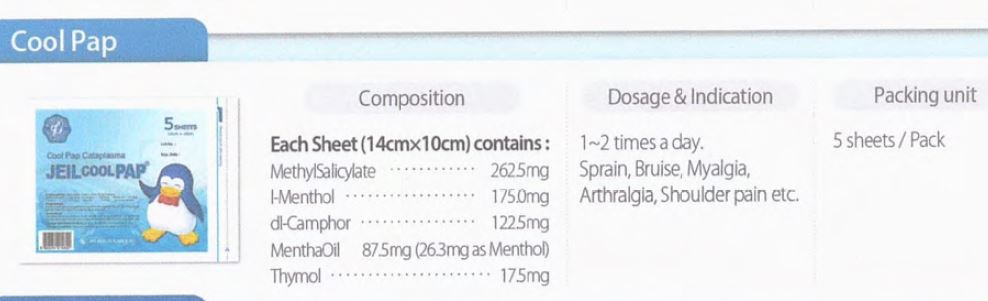 DRUG LABEL: Cool Pap Cataplasma
NDC: 72988-0008 | Form: PATCH
Manufacturer: Lydia Co., Ltd.
Category: otc | Type: HUMAN OTC DRUG LABEL
Date: 20220117

ACTIVE INGREDIENTS: THYMOL 17.5 mg/17.5 g; PEPPERMINT OIL 87.5 mg/17.5 g; LEVOMENTHOL 17.5 mg/17.5 g; CAMPHOR (SYNTHETIC) 122.5 mg/17.5 g; METHYL SALICYLATE 262.5 mg/17.5 g
INACTIVE INGREDIENTS: KAOLIN

Drug Facts

ACTIVE INGREDIENT

Methyl salicylate

ℓ-Menthol

dl-Camphor

Mentha oil

Thymol

INACTIVE INGREDIENT

Kaolin

Zinc oxide

Titanium oxide

Gelatin

Glycerin

Liquid paraffin

Carboxymethylcellulose sodium

Polybutene

Sodium polyacrylate

Butylated hydroxy toluene

Polysorbate 60

Methoxyethylene maleicanhydride copolymer

Citric acid hydrate

Natural rubber latex

Purified water

Nonwoven fabric

Polyester film

PURPOSE

Topical Analgesic

Temporarily relieves minor pain associated with - muscular pain - joint pain - backache - bruise - sprain

keep out of reach of the children

INDICATIONS AND USAGE

Adults and children 12 years of age and over: apply to affected area not more than 3 to 4 times daily.

Children under 12 years of age: do not use, consult a doctor
For easy application: partially peel back protective film and apply exposed patch to the site of pain.
Carefully remove remaining film while pressing patch to skin for secure adhesion.

WARNINGS

use only as directed
do not bandage tightly or use with a healing pad
avoid contact with the eyes and mucous membranes
do not apply to wounds or damaged skin

DOSAGE AND ADMINISTRATION

for external use only